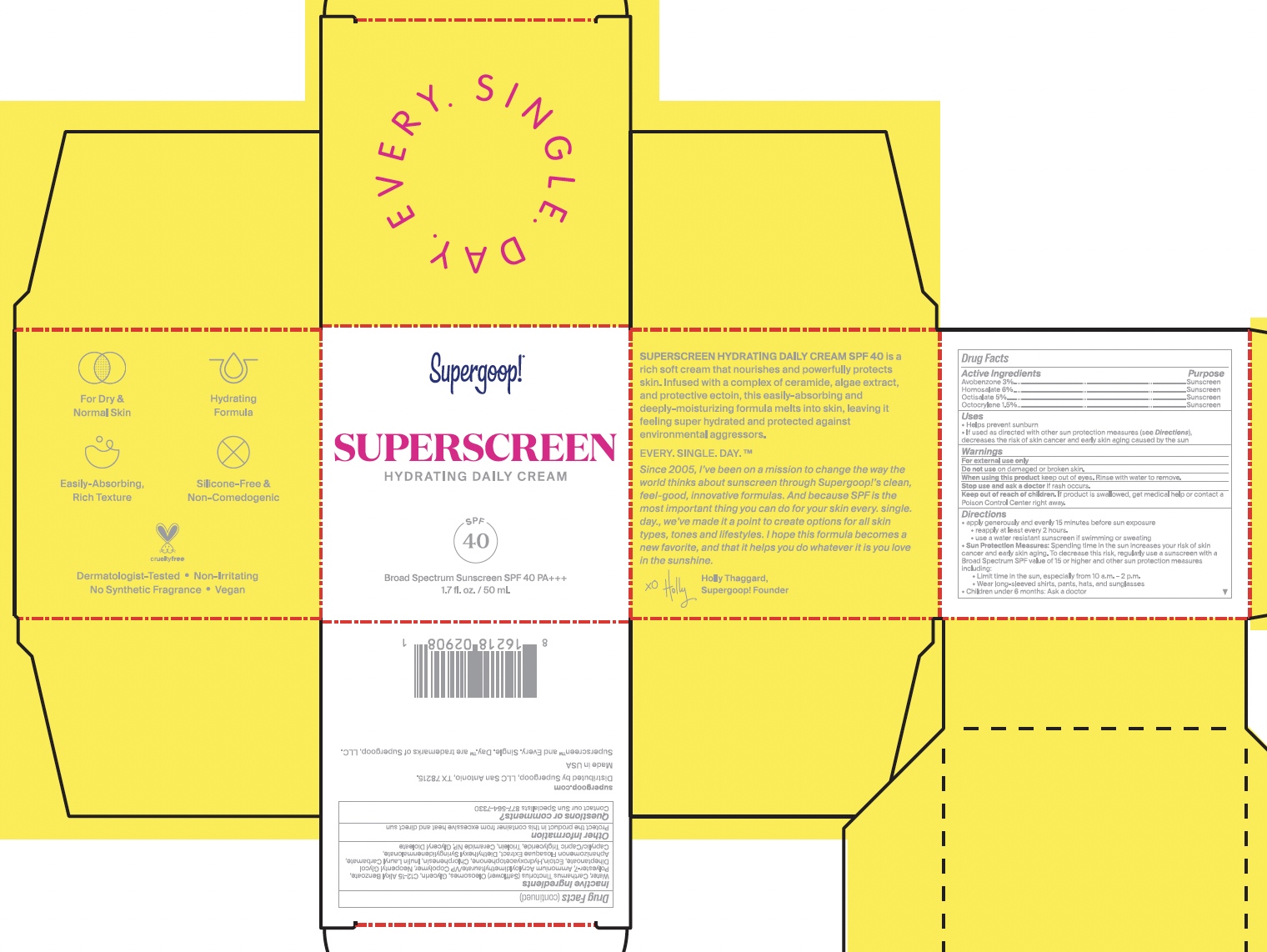 DRUG LABEL: Superscreen Hydrating Daily Cream SPF 40
NDC: 75936-620 | Form: CREAM
Manufacturer: Supergoop, LLC
Category: otc | Type: HUMAN OTC DRUG LABEL
Date: 20230626

ACTIVE INGREDIENTS: HOMOSALATE 6 g/100 mL; OCTOCRYLENE 1.5 g/100 mL; AVOBENZONE 3 g/100 mL; OCTISALATE 5 g/100 mL
INACTIVE INGREDIENTS: CARTHAMUS TINCTORIUS (SAFFLOWER) OLEOSOMES; ALKYL (C12-15) BENZOATE; ECTOINE; MEDIUM-CHAIN TRIGLYCERIDES; GLYCERYL TRIOLEATE; INULIN LAURYL CARBAMATE; WATER; POLYESTER-7; AMMONIUM ACRYLOYLDIMETHYLTAURATE/VP COPOLYMER; HYDROXYACETOPHENONE; CHLORPHENESIN; APHANIZOMENON FLOSAQUAE; GLYCERYL DIOLEATE; NEOPENTYL GLYCOL DIHEPTANOATE; DIETHYLHEXYL SYRINGYLIDENEMALONATE; CERAMIDE NP; GLYCERIN

Superscreen Hydrating Daily Cream SPF 40

ACTIVE INGREDIENT

Active Ingredients: Avobenzone 3%, Homosalate 6%, Octisalate 5%, Octocrylene 1.5%

PURPOSE

Helps prevent sunburn

If used as directed with other sun protection measures (see Directions), decreases the risk of skin cancer and early skin aging caused by the sun

Keep out of reach of children. If product is swallowed, get medical help, or contact a poison control center right away.

WARNINGS

For External use only

Do not use on damaged or broken skin

When using this product, keep out of eyes. Rinse with water to remove

Stop use and ask a doctor if rash occurs

Directions

Apply generously and evenly 15 minutes before sun exposure

Reapply at least every 2 hours

Use a water resistant sunscreen if swimming or sweating

Sun Protection Measures: Spending time in the sun increases your risk of skin cancer and early skin aging. To decrease this risk, regularly use a sunscreen with a Broad Spectrum SPF value of 15 or higher and other sun protection measures including:

Limit time in the sun, especially from 10 a.m.- 2 p.m.

Wear long-sleeved shirts, pants, hats, and sunglasses

Children under 6 months: Ask a doctor

PACKAGE LABEL

Superscreen Hydrating Daily Cream SPF 40 / 50 mL